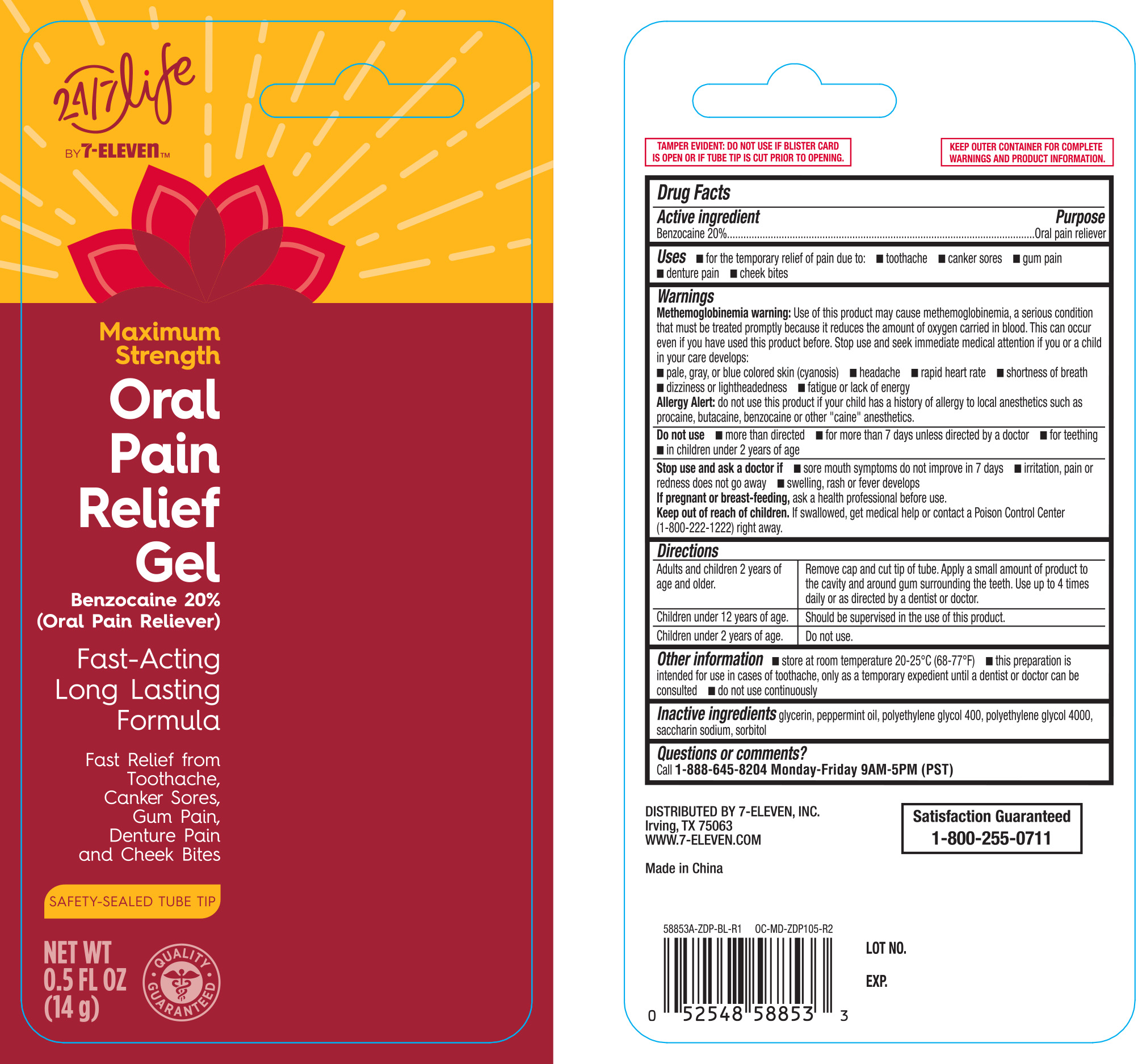 DRUG LABEL: 7 Select Oral Pain Maximum Strength Relief
NDC: 10202-853 | Form: GEL
Manufacturer: 7-ELEVEN, INC.
Category: otc | Type: HUMAN OTC DRUG LABEL
Date: 20251031

ACTIVE INGREDIENTS: BENZOCAINE 200 mg/1 g
INACTIVE INGREDIENTS: POLYETHYLENE GLYCOL 400; POLYETHYLENE GLYCOL 4000; SACCHARIN SODIUM; SORBITOL; GLYCERIN; MINT

24/7 Life Oral Pain Relief Gel 0.5 oz (58853A)

Active ingredient Purpose

Benzocaine 20%.................................Oral Pain reliever

PURPOSE

Use for the temporary relief of pain due to:

- toothache
- canker sores
- gum pain
- denture pain
- cheek bites

Warnings

Methemoglobinemia warning: Use of this product may cause methemoglobinemia, a serious condition that must be treated promptly because it reduces the amount of oxygen carried in blood. This can occur even if you have used this product before. Stop use and seek immediate meddical attention if you or a child in your care develops:

- pale, gray, or blue colored skin (cyanosis)
- headache
- rapid heart rate
- shortness of breath
- dizziness or lightheadedness
- fatigue or lack of energy

Allergy alert: do not use this product if you have a history of allergy to local anesthetics such as procaine, butacaine, benzocaine or other "caine" anesthetics

Do not use

- more than directed
- for more than 7 days unless directed by a dentist or doctor
- for teething
- in children under 2 years of age

Stop use and ask a doctor if

- sore mouth symptoms do not improve in 7 days
- swelling, rash or fever develops
- irritation, pain or redness persists or worsens

PREGNANCY OR BREAST FEEDING

If pregnant or breast-feeding, ask a health professional before use.

Keep out of reach of children.

If swallowed, get medical help or contact a Poison Control Center (1-800-222-1222) right away.

Directions

Adults and children 2 years of age and older. | Remove cap and cut tip of tube. Apply a small amount of product to the cavity and around gum surrounding the teeth. Use up to 4 times daily or as directed by a dentist or dentist.
Children under 12 years of age. | Should be supervised in the use of this product.
Children under 2 years of age. | Do not use.

Other information

- store at 20° to 25°C (68° to 77°F)
- this preparation is intended for use in cases of toothache, only as a temporary expedient until a dentist or doctor can be consulted
- do not use continuously

INACTIVE INGREDIENT

Inactive ingredients glycerin, peppermint oil, polyethylene glycol 400, polyethylene glycol 4000, saccharin sodium, sorbitol

DOSAGE AND ADMINISTRATION

DISTRIBUTED BY 7-ELEVEN, INC.

Irving, TX 75063

WWW.7-ELEVEN.COM